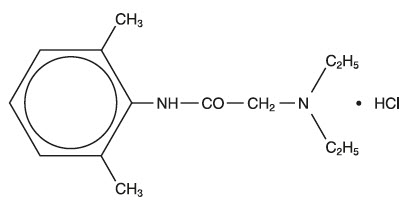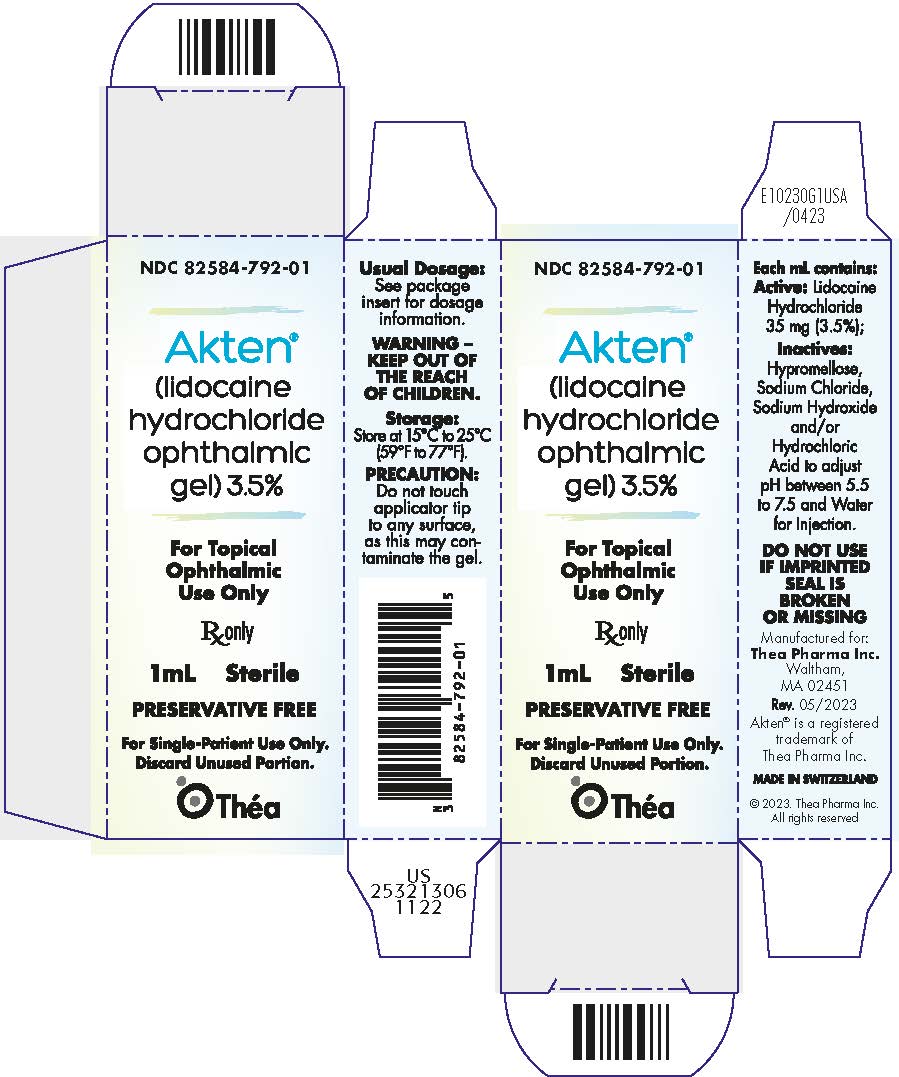 DRUG LABEL: AKTEN
NDC: 82584-792 | Form: GEL
Manufacturer: Thea Pharma Inc.
Category: prescription | Type: HUMAN PRESCRIPTION DRUG LABEL
Date: 20251208

ACTIVE INGREDIENTS: LIDOCAINE HYDROCHLORIDE ANHYDROUS 35 mg/1 mL
INACTIVE INGREDIENTS: SODIUM CHLORIDE; SODIUM HYDROXIDE; HYDROCHLORIC ACID; WATER; HYPROMELLOSE, UNSPECIFIED

HIGHLIGHTS OF PRESCRIBING INFORMATION

These highlights do not include all the information needed to use AKTEN® safely and effectively. See full prescribing information for Akten®.
AKTEN® (lidocaine hydrochloride ophthalmic gel), for topical ophthalmic use.
Initial U.S. Approval: 1972

1 INDICATIONS AND USAGE

AKTEN is an amide local anesthetic indicated for ocular surface anesthesia during ophthalmologic
procedures. (1)

2 DOSAGE AND ADMINISTRATION

The recommended dose of AKTEN is 2 drops applied to the ocular surface in the area of the planned procedure. AKTEN may be reapplied to maintain anesthetic effect. (2)

3 DOSAGE FORMS AND STRENGTHS

Ophthalmic Gel: 3.5% lidocaine hydrochloride in single-patient-use tubes. (3)

4 CONTRAINDICATIONS

None. (4)

5 WARNINGS AND PRECAUTIONS

- For Topical Ophthalmic Use: AKTEN is not for injection or intraocular administration. (5.1)
- Patients should not touch the eye for at least 10 to 20 minutes after using AKTEN as accidental injuries can occur due to insensitivity of the eye. (5.2)
- Corneal Opacification: Prolonged use of a topical ocular anesthetic may produce permanent corneal opacification and ulceration with accompanying visual loss. (5.2)
- For Administration by Healthcare Provider: AKTEN is not intended for patient self-administration. (5.3)

6 ADVERSE REACTIONS

Most common adverse reactions are conjunctival hyperemia, corneal epithelial changes, headache, and burning upon instillation. (6)

To report SUSPECTED ADVERSE REACTIONS, contact Thea Pharma Inc. at 1-833-838-4028 or FDA at 1-800-FDA-1088 or www.fda.gov/medwatch.

See 17 for PATIENT COUNSELING INFORMATION.

FULL PRESCRIBING INFORMATION

1 INDICATIONS AND USAGE

AKTEN is indicated for ocular surface anesthesia during ophthalmologic procedures in adults and pediatric patients.

2 DOSAGE AND ADMINISTRATION

The recommended dose of AKTEN is 2 drops applied to the ocular surface in the area of the planned procedure. AKTEN may be reapplied to maintain anesthetic effect.

3 DOSAGE FORMS AND STRENGTHS

Ophthalmic Gel: 3.5% lidocaine hydrochloride in single-patient use tubes.

4 CONTRAINDICATIONS

None.

5 WARNINGS AND PRECAUTIONS

.

5.1 For Topical Ophthalmic Use

AKTEN is not for injection or intraocular administration.

5.2 Corneal Injury Due to Insensitivity

Patients should not touch the eye for at least 10 to 20 minutes after using AKTEN as accidental injuries can occur due to insensitivity of the eye.

5.3 Corneal Opacification

Prolonged use of a topical ocular anesthetic may produce permanent corneal opacification and ulceration with accompanying visual loss.

5.4 For Administration by Healthcare Provider

AKTEN is indicated for administration under the direct supervision of a healthcare provider.

AKTEN is not intended for patient self-administration.

6 ADVERSE REACTIONS

Most common adverse reactions are conjunctival hyperemia, corneal epithelial changes, headache, and burning upon instillation.

8 USE IN SPECIFIC POPULATIONS

.

8.1 Pregnancy

Risk Summary

There are no adequate and well-controlled studies with AKTEN in pregnant women to inform a drug-associated risk. In animal reproduction studies, subcutaneous administration of lidocaine to pregnant rats at doses >800-fold the human dose based on body surface area did not result in adverse developmental effects.

The estimated background risk of major birth defects and miscarriage for the indicated population(s) is unknown. All pregnancies have a background risk of birth defect, loss, or other adverse outcomes. In the U.S. general population, the estimated background risk of major birth defects and miscarriage in clinically recognized pregnancies is 2 to 4% and 15 to 20%, respectively.

8.2 Lactation

Risk Summary
Lidocaine is secreted in human milk. The clinical significance of this observation is unknown. Caution should be exercised when AKTEN is administered to a nursing woman.

8.4 Pediatric Use

The safety and effectiveness of AKTEN for ocular surface anesthesia during ophthalmologic procedures have been established in pediatric patients. Use of AKTEN for this indication has been extrapolated from adequate and well-controlled studies in adults and studies in pediatric patients using different formulations of lidocaine.

8.5 Geriatric Use

No overall clinical differences in safety or effectiveness were observed between the elderly and other adult patients.

10 OVERDOSAGE

Prolonged use of a topical ocular anesthetic may produce permanent corneal opacification and ulceration with accompanying visual loss.

Acute emergencies from local anesthetics are generally related to high plasma levels encountered during therapeutic use of local anesthetics or to unintended subarachnoid injection of local anesthetic solution. However, topical ocular application of AKTEN is not expected to result in systemic exposure.

11 DESCRIPTION

AKTEN (lidocaine hydrochloride ophthalmic gel) 3.5% contains lidocaine hydrochloride, an amide local anesthetic, as a sterile ophthalmic gel for topical ophthalmic use. AKTEN does not contain an anti-microbial preservative. Lidocaine hydrochloride is designated chemically as acetamide, 2-(diethylamino)-N-(2,6-dimethylphenyl) monohydrochloride with a molecular formula of C14H22N2O ∙ HCl and molecular weight of 270.8. The structural formula of the active ingredient is:

Each mL of AKTEN contains 35 mg of lidocaine hydrochloride as the active ingredient. Inactive ingredients: hypromellose, sodium chloride, and water for injection.

The pH may be adjusted to 5.5 to 7.5 with hydrochloric acid and/or sodium hydroxide. AKTEN does not contain an anti-microbial preservative.

12 CLINICAL PHARMACOLOGY

12.1 Mechanism of Action

Lidocaine hydrochloride is an amide local anesthetic agent that stabilizes the neuronal membrane by inhibiting the ionic fluxes required for the initiation and conduction of impulses, thereby effecting local anesthetic action. Anesthesia generally occurs between 20 seconds to 1 minute and persists for 5 to 30 minutes.

12.3 Pharmacokinetics

Lidocaine may be absorbed following topical administration to mucous membranes. Its rate and extent of absorption depend upon various factors such as concentration, the specific site of application, viscosity of the agent, and duration of exposure.

The plasma binding of lidocaine is dependent on drug concentration, and the fraction bound decreases with increasing concentration. At concentrations of 1 to 4 mcg of free base per mL, 60 to 80 percent of lidocaine is protein bound. Binding is also dependent on the plasma concentration of the alpha-1-acid glycoprotein. Lidocaine is metabolized rapidly by the liver, and metabolites and unchanged drug are excreted by the kidneys. Biotransformation includes oxidative N- dealkylation, ring hydroxylation, cleavage of the amide linkage, and conjugation. N-dealkylation, a major pathway of biotransformation, yields the metabolites monoethylglycinexylidide and glycinexylidide. The pharmacologic/toxicologic actions of these metabolites are similar to, but less potent than, those of lidocaine. Approximately 90% of lidocaine administered is excreted in the form of various metabolites, and less than 10% is excreted unchanged. The primary metabolite in urine is a conjugate of 4-hydroxy-2, 6-dimethylaniline.

Studies of lidocaine metabolism following intravenous bolus injections have shown that the elimination half-life of this agent is typically 1.5 to 2 hours. Because of the rate at which lidocaine is metabolized, any condition that affects liver function may alter lidocaine kinetics. The half-life may be prolonged twofold or more in patients with liver dysfunction. Renal dysfunction does not affect lidocaine kinetics but may increase the accumulation of metabolites.

13 NONCLINICAL TOXICOLOGY

13.1 Carcinogenesis, Mutagenesis, Impairment of Fertility

Long-term studies in animals have not been performed to evaluate the carcinogenic potential of AKTEN .

14 CLINICAL STUDIES

The effect of AKTEN® on ocular anesthesia was studied in a multi-center, randomized, controlled, double-blind study. A total of 209 subjects were enrolled, with 54, 51, 53, and 51 subjects randomized to the sham, AKTEN® 1.5%, AKTEN® 2.5%, and AKTEN® 3.5% groups, respectively. Ocular anesthesia was achieved within 5 minutes of anesthetic application by 47 of 51 subjects (92%) in the AKTEN® 3.5% group.

The mean time to anesthesia onset ranged from 20 seconds to 5 minutes and was not affected by AKTEN® dose. The mean time to anesthesia onset was approximately 60 seconds, with a median onset time of 40 seconds for the AKTEN® 3.5% group. Among the subjects in the AKTEN® groups who achieved anesthesia within 5 minutes, approximately 90% had achieved anesthesia within 60 seconds of application.

The duration of anesthesia generally ranged from approximately 5 minutes to 30 minutes, with mean anesthesia durations of approximately 15 minutes for the AKTEN® 3.5% group.

Approximately 84% of the subjects in the AKTEN® 3.5% group experienced anesthesia for at least 5 minutes, approximately 55% of subjects experienced anesthesia for 10 minutes or longer and 27% experienced anesthesia for 15 minutes or longer. The anesthetic effect of additional applications of AKTEN® has not been evaluated.

16 HOW SUPPLIED/STORAGE AND HANDLING

AKTEN (lidocaine hydrochloride ophthalmic gel) 3.5% is supplied as a clear gel in single-patient-use tubes as follows:

NDC 82584-792-01 | 1 mL fill in a white polyfoil tube [Made in Switzerland]
NDC 82584-792-25 | Package of 25 units of 1 mL fill in a white polyfoil tube

Storage

Store at 15°C to 25°C (59°F to 77°F).

Keep single-patient-use tubes closed and protected from light in the original carton until ready for use. Discard after use.

17 PATIENT COUNSELING INFORMATION

Eye Care Precaution
Advise patients to avoid touching the eye for at least 10 to 20 minutes after using AKTEN as accidental injuries can occur due to insensitivity of the eye.

Manufactured for: Thea Pharma Inc.
Waltham, MA 02451
Made in Switzerland
Patented [US8759401]
© 2025. Thea Pharma Inc. All rights reserved

Revised: 11/2025

Thea Pharma Inc.

PRINCIPAL DISPLAY PANEL - 1 mL Tube Carton

NDC 82584-792-01

Akten®

(lidocaine
hydrochloride
ophthalmic
gel) 3.5%

For Topical
Ophthalmic
Use Only

Rx only

1mL
Sterile

PRESERVATIVE FREE

For Single-Patient Use Only.
Discard Unused Portion.

Théa